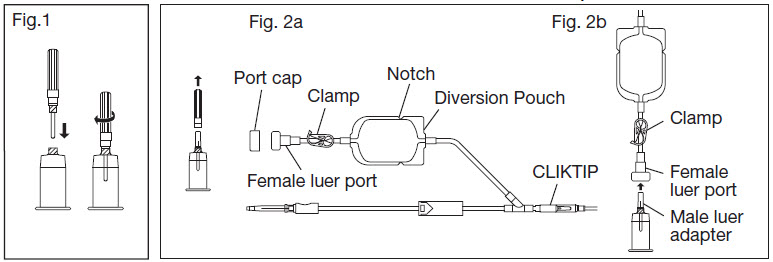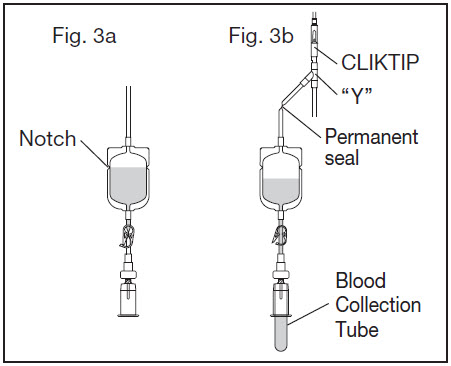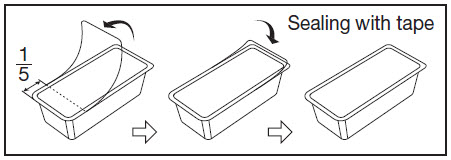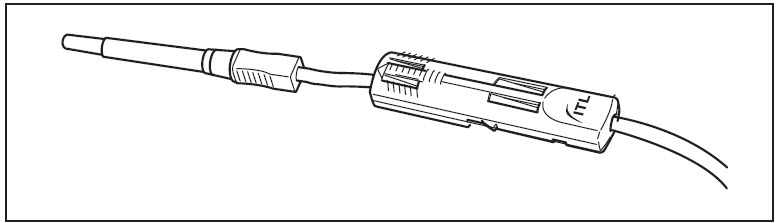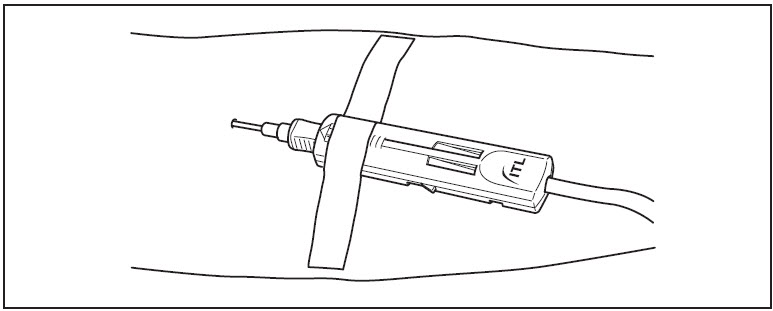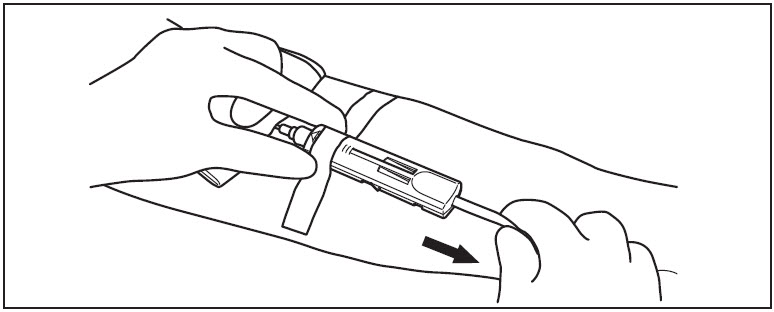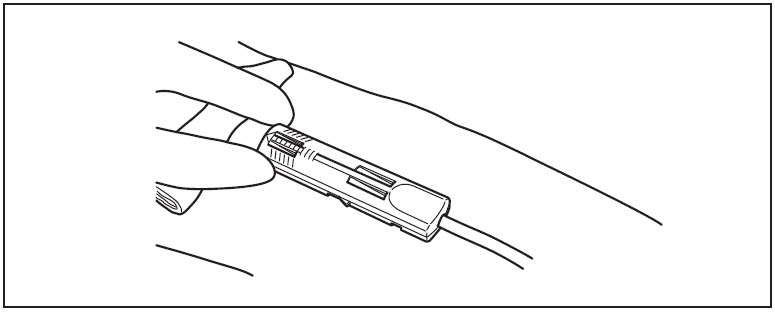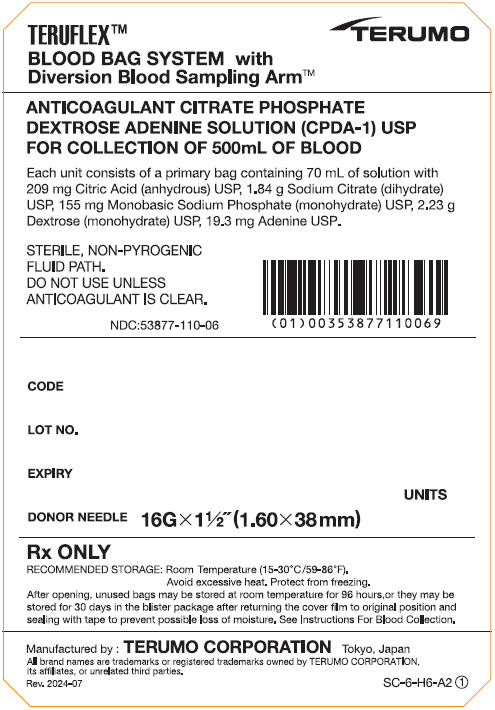 DRUG LABEL: teruflex blood bag system with diversion blood sampling arm 70 ml cpda-1
NDC: 53877-110 | Form: SOLUTION
Manufacturer: Terumo Corporation
Category: prescription | Type: HUMAN PRESCRIPTION DRUG LABEL
Date: 20241010

ACTIVE INGREDIENTS: Anhydrous Citric Acid 2.99 g/1000 mL; Trisodium Citrate Dihydrate 26.3 g/1000 mL; Sodium Phosphate, Monobasic, Monohydrate 2.22 g/1000 mL; Dextrose Monohydrate 31.9 g/1000 mL; Adenine 0.275 g/1000 mL
INACTIVE INGREDIENTS: Water

TERUFLEX™ BLOOD BAG SYSTEM with Diversion Blood Sampling Arm™
CPDA-1 SOLUTION
For the collection of 450 mL or 500 mL of Whole Blood

Rev. 2020-09
N-BB-CA-A-DB ④

FULL PRESCRIBING INFORMATION

*Sections or subsections omitted from the Full Prescribing Information are not listed [includes sections 4, 6, 7, 8, 9, 10, 12, 13, 14, 15 and 17].

1. INDICATIONS AND USAGE

1.1. Read these instructions carefully before use.

1.2. Rx ONLY.

1.3. Intended for the collection, processing and preservation of Whole Blood and blood components. Not intended for direct intravenous infusion.

1.4. For the collection of 450 mL ±10% or 500 mL ±10% Whole Blood.

1.5. Integral Diversion Blood Sampling Arm is intended to divert and obtain donor samples for laboratory testing prior to collection of the Whole Blood unit.

1.6. For further processing, use standard component processing techniques.

2. DOSAGE AND ADMINISTRATION

2.1. To open blister package, peel cover film back 4/5 of its length.

2.2. Prepare the blood bag following your institution's standard operating procedures.

2.2.1. Materials Needed:

- VENOJECT II Tube Holder (code P-1316R) or equivalent
- VENOJECT II Multi-Sample Luer Adapter (code MN*2000T) or equivalent
- Evacuated blood collection tubes (glass or plastic)

2.3. Make a loose knot in the donor tubing below the "Y" and CLIKTIP (inline closure device) unless alternate methods are used to seal the tubing at the end of collection.

2.4. Temporarily clamp donor tubing between the phlebotomy needle and the "Y".

2.5. Close the White Clamp below the diversion pouch.

2.6. Assemble the luer adapter and the tube holder.

2.6.1. Connect the VENOJECT II Multi-Sample Luer Adapter to the VENOJECT II Tube Holder (or equivalent) (Fig. 1).

2.6.2. Twist and snap to remove the blue port cap at the end of the Diversion Blood Sampling Arm (Fig. 2a).

2.6.3. Insert the Holder/Luer assembly in the female luer port (Fig. 2b).

2.6.4. NOTE: Alternatively, steps 2.6.1., 2.6.2., and 2.6.3. (above) may be performed at any time during bag preparation or after the blood is collected into the diversion pouch.

2.7. Suspend the collection bag as far as possible below the donor's arm.

2.8. Apply blood pressure cuff or tourniquet to donor's arm. Disinfect site of phlebotomy according to institutional standard operating procedures. If blood pressure cuff is used, inflate to approximately 60 mmHg.

2.9. Remove the needle cover and perform phlebotomy. Remove the temporary clamp on the donor tubing to permit blood flow into the Diversion Blood Sampling Arm pouch.

2.9.1. CAUTION: Do not touch the needle after removing the needle cover.

2.9.2. CAUTION: Assure that the White Clamp below the pouch is closed prior to initiating phlebotomy.

2.10. Secure the needle safety device in place following the device instructions provided on the reverse side.

2.11. Secure donor tubing to donor's arm.

2.12. Position the diversion pouch with the notches up and the Tube Holder/Luer Adapter assembly (or port cap) down. When the level of blood in the pouch is approximately in line with the notches, the diversion pouch is full (Fig. 3a).

2.12.1. NOTE: The approximate fill volume of the pouch at the notches is 35 mL.

2.13. Permanently seal the tubing between the "Y" and the diversion pouch to maintain a closed system using an aluminum clip or a tube sealer approved for use with tubing connected to a donor (Fig. 3b).

2.13.1. CAUTION: Do not use a dielectric tube sealer to seal the tubing while the needle is connected to the donor's body unless it is approved for such a purpose.

2.14. To initiate blood flow into the collection bag, break the CLIKTIP between the "Y" and the collection bag.

2.15. To avoid clot formation, collect samples as soon as possible from the diversion pouch as follows (Fig. 3b).

2.15.1. CAUTION: Do not collect donor test samples until the tubing between the "Y" and the diversion pouch is permanently sealed.

2.15.2. Open the White Clamp on the tubing below the pouch to open the pathway for sampling.

2.15.3. Position the diversion pouch with the notches up and the Tube Holder/Luer Adapter assembly downward. Assure that any air in the pouch is at the top and will not enter the blood collection tubes.

2.15.4. Insert blood collection tube firmly into the tube holder; when full, remove sample tube from holder. Repeat to collect additional samples.

2.15.5. NOTE: The pouch may be removed after the donor test samples are collected. A second seal must be made between the diversion pouch and the permanent seal prior to removing the pouch.

2.16. Mix blood with anticoagulant in the collection bag and continue to mix at several intervals during collection and immediately after collection. If using an automated mixer, follow manufacturer's instructions.

2.17. Collect labeled volume of blood 450 mL ±10% or 500 mL ±10%.

2.18. When the desired amount of blood has been collected, seal the tubing or tighten the loose knot (white knot) prepared in Step 2.3. Make a second seal between the first seal or knot and the "Y". Various methods may be used to seal tubing.

2.19. Release pressure on the donor's arm and remove the needle into the needle safety device following the device instructions provided on the reverse side. Sever the donor tubing between the two seals previously made below the CLIKTIP and "Y".

2.19.1. CAUTION: Discard the Diversion Blood Sampling Arm and phlebotomy needle/donor tubing according to institutional standard operating procedures.

2.20. Strip blood from donor tubing into collection bag, mix well, and allow tubing to refill; repeat once. To prevent the blood from clotting in the tubing, work quickly as possible. Make an appropriate number of segments of anticoagulated blood for testing by sealing on or near the X marks. Leave segments attached to the Whole Blood unit.

2.21. The time between Whole Blood collection and component separation may vary depending on both the blood bag system and processing options selected. Follow your institution's standard operating procedures to prepare components.

2.21.1. If the Whole Blood is to be processed into room temperature components, maintain the blood at ambient temperature.

2.21.2. If the Whole Blood is to be processed into other components (including Plasma Frozen Within 24 Hours After Phlebotomy), Whole Blood must either be placed in storage at a temperature between 1-6°C within 8 hours of blood collection or cooled towards a temperature between 1-10°C (e.g. during transport) and then placed in storage at a temperature between 1-6°C upon arrival at the processing center.

2.22. Platelet Rich Plasma and Platelets should be separated from the Red Blood Cells within 8 hours of blood collection, if prepared.

2.23. Plasma intended for production of Fresh Frozen Plasma should be separated from the Red Blood Cells and placed in a freezer at –18°C or colder within 8 hours of blood collection.

2.24. Plasma intended for production of Plasma Frozen Within 24 Hours After Phlebotomy (PF24) should be placed in a freezer at -18°C or colder within 24 hours of blood collection.

2.25. For further preparation and processing of other plasma components, use standard processing and storage techniques following approved regulations and standards.

2.26. Select the appropriate spin condition and centrifuge Whole Blood unit to separate CPDA-1 Red Blood Cells from plasma or platelet rich plasma, as appropriate.

2.27. Break the CLIKTIP of primary collection bag and transfer plasma into satellite bag, or transfer platelet rich plasma into XT-612 Platelet bag. Clamp transfer tubing of satellite bag.

2.28. Seal tubing of primary collection bag in two places, cut between seals, and if applicable, separate from satellite bag(s).

2.29. Store CPDA-1 Red Blood Cells (or Whole Blood) between 1 – 6°C for up to 35 days.

2.30. If prepared, store Platelets between 20-24°C, maintaining a continuous gentle agitation, for up to 5 days in XT-612 bag.

3. DOSAGE FORMS AND STRENGTHS

3.1. 63 mL Citrate Phosphate Dextrose Adenine (CPDA-1) anticoagulant USP for collection of 450 mL Whole Blood. Each 63 mL contains 188 mg Citric Acid (anhydrous) USP, 1.66 g Sodium Citrate (dihydrate) USP, 140 mg Monobasic Sodium Phosphate (monohydrate) USP, 2.01 g Dextrose (monohydrate) USP and 17.3 mg Adenine USP.

3.2. 70 mL Citrate Phosphate Dextrose Adenine (CPDA-1) anticoagulant USP for collection of 500 mL Whole Blood. Each 70 mL contains 209 mg Citric Acid (anhydrous) USP, 1.84 g Sodium Citrate (dihydrate) USP, 155 mg Monobasic Sodium Phosphate (monohydrate) USP, 2.23 g Dextrose (monohydrate) USP and 19.3 mg Adenine USP.

5. WARNINGS AND PRECAUTIONS

5.1. Rx ONLY.

5.2. Do not use unless solutions are clear and free from particulates.

5.3. Always inspect the blood bag set for leaks before use.

5.4. Avoid excessive heat and direct sunlight. Protect from freezing.

5.5. Recommended storage conditions: Room Temperature (15-30°C/59-86°F).

5.6. It is normal to have condensation in the blister packaging. If the amount of moisture is greater than expected, check for leaks from the fluid-filled components of the blood bag set.

5.7. Use aseptic techniques.

5.8. Do not use a dielectric tube sealer to seal the tubing while the needle is connected to the donor's body unless it is approved for such a purpose.

5.9. Do not touch needle after removing the needle cover.

5.10. Assure that the White Clamp below the pouch is closed prior to initiating phlebotomy.

5.11. Do not collect donor test samples until the tubing between the "Y" and the diversion pouch is permanently sealed.

5.12. Discard the Diversion Blood Sampling Arm and phlebotomy needle/donor tubing according to institutional standard operating procedures.

5.13. The AGELESS oxygen absorber packet, (Mitsubishi Gas Chemical) contained in this package absorbs oxygen and generates heat on removal. Do not open and handle it with care.

5.14. Dispose of the AGELESS packet with the blister tray.

5.15. Do not dispose the AGELESS packet with wastes containing volatile or flammable materials.

5.16. Due to possible exposure to infectious agents in the handling of blood, take adequate precautions at all times to prevent exposure to and transmission of such agents. Follow your institution's standard operating procedures.

11. DESCRIPTION / PRODUCT SPECIFICATIONS

11.1. This blood bag system includes a 16 gauge × 1 1/2 inch (1.60 × 38 mm) needle with needle cover and either a 450 mL or 500 mL (nominal capacity 600 mL) primary collection bag containing 63 mL or 70 mL, respectively, Citrate Phosphate Dextrose Adenine (CPDA-1) anticoagulant. The Triple blood bag set has one integrally attached empty satellite bag (nominal capacity 400 mL) and one empty XT-612 5 day Platelet bag (nominal capacity 500 mL). The Quadruple blood bag set has two integrally attached empty satellite bags (nominal capacity 400 mL) and one empty XT-612 5 day Platelet bag (nominal capacity 500 mL).

11.2. Blood bag codes ending in A2 are supplied with Integral Diversion Blood Sampling Arm intended to divert and obtain donor samples for laboratory testing prior to collection of the Whole Blood unit.

11.3. Blood bag codes ending in A2 also include a DonorCare Needle Guard pre-attached to the donor tubing. DonorCare Needle Guard device instructions are provided on the reverse side.

11.4. The blood bag collection set is made of PVC (polyvinyl chloride with DEHP plasticizer).

11.5. The blood bag has no components made of natural rubber latex.

11.6. Tubing internal diameter (ID) nominal 3.0 mm.

11.7. Tubing outer diameter (OD) nominal 4.4 mm.

11.8. Donor tubing line maximum 16 segments available.

16. HOW SUPPLIED/STORAGE AND HANDLING

16.1. Single use only.

16.2. Sterile and non-pyrogenic fluid path. Sterilized by steam. Opacity of the blood bag system may be observed. This is due to moisture absorption during the sterilization process. This is normal and does not affect the solution quality or safety. The opacity will diminish gradually.

16.3. A Material Safety Data Sheet (MSDS) is not required for this product.

STORAGE AND HANDLING

16.4. Recommended storage conditions: Room Temperature (15-30°C/59-86°F).

16.5. Avoid excessive heat and direct sunlight. Protect from freezing.

16.6. To open blister package, peel cover film back 4/5 of its length.

16.7. After opening the blister package, unused blood bags may be stored at room temperature for 96 hours or they may be stored for 30 days by returning cover film to original position and sealing with tape to prevent evaporation of solutions.

16.8. Blood bags in the unopened blister package may be used through the last day of the month and year as indicated on the original manufacturer's packaging.

16.9. The AGELESS packet contained in this package absorbs oxygen and generates heat on removal. Do not open and handle it with care.

16.10. Dispose of the AGELESS packet with the blister tray.

16.11. Do not dispose the AGELESS packet with wastes containing volatile or flammable materials.

16.12. For the Triple blood bag sets, Codes BB*TCD456A2 and BB*TCD506A2 are supplied 30/case.

16.13. For the Quadruple blood bag sets, Codes BB*QCD456A2 and BB*QCD506A2 are supplied 24/case.

MANUFACTURED BY:
TERUMO CORPORATION
44-1, 2-CHOME, HATAGAYA, SHIBUYA-KU,
TOKYO 151-0072, JAPAN MADE IN JAPAN

© TERUMO CORPORATION Mar. 2021

All brand names are trademarks or registered trademarks of TERUMO CORPORATION and their respective owners.

PROCEDURE FOR USE OF DonorCare™ Needle Guard

This device is for use by trained individuals.

Intended Use

The DonorCare Needle Guard is incorporated onto the donor tubing to shield the needle immediately after withdrawal from the donor.

Single Use Only.

Preparation

1. Move the DonorCare on the tubing ensuring that it slides easily and the arrow is pointing toward the needle hub.

2. Ensure that the three lock points on the DonorCare are locked closed.

Whole Blood Collection

3. Perform the phlebotomy as per your institution's standard operating procedures.

4. Slide the DonorCare over the needle hub so that it covers approximately one half to two thirds of the needle hub.

5. Stabilize the DonorCare to the arm by placing a piece of tape over the front end so that the tape does not extend over the front of the DonorCare.

Withdrawal of Needle

Important | The DonorCare must be held stationary while the needle is withdrawn into it.
Caution | The needle must be fully shielded by DonorCare to prevent accidental injury.

6. Hold gauze over the venipuncture site with finger tips without exerting pressure. Hold the sides of the DonorCare near the front with the index finger and thumb of the same hand.

7. With the other hand, hold the donor tubing close behind the DonorCare.

Note: A hemostat may be placed on the tubing behind the DonorCare when the blood collection is complete. This will help to prevent blood drops from forming.

8. Pull tubing smoothly and swiftly with one motion until the needle is locked in place inside the DonorCare.

9. Confirm that the needle is locked by:

1. Listening for two 'clicks' as the needle is drawn into DonorCare.
2. If the clicks are not heard as the needle is drawn into the DonorCare, continue to pull firmly on the tubing to assure needle is fully withdrawn into DonorCare.

10. Visually check that the needle is fully shielded by DonorCare before removing from the donor's arm.

11. Remove the tape from the DonorCare and arm.

12. Apply pressure to the gauze covering the venipuncture site.

Warning | Do not place fingers at the opening of DonorCare after removal from the donor's arm.

Difficult Phlebotomy (Examples may include: Slow blood flow, deep or fine vein, steep angle)

It may be necessary to delay placing the DonorCare over the needle hub until the end of the blood collection. In such situations:

Leave the DonorCare on the tubing behind the needle hub. At the end of the blood collection carefully remove the tape from the needle hub and slide the DonorCare over the hub so that it covers approximately one half to two thirds of the needle hub.

Withdraw the needle into the DonorCare as stated in steps 6. through 12. above.

Rx ONLY

DonorCare is manufactured by ITL Corporation, Melbourne, Australia.

TERUMO CORPORATION
44-1, 2-CHOME, HATAGAYA, SHIBUYA-KU,
TOKYO 151-0072, JAPAN

© TERUMO CORPORATION Mar. 2021

PRINCIPAL DISPLAY PANEL - 70 mL Bag Blister Pack Case Label

TERUFLEX™
BLOOD BAG SYSTEM with
Diversion Blood Sampling Arm™

TERUMO

ANTICOAGULANT CITRATE PHOSPHATE
DEXTROSE ADENINE SOLUTION (CPDA-1) USP
FOR COLLECTION OF 500mL OF BLOOD

Each unit consists of a primary bag containing 70 mL of solution with
209 mg Citric Acid (anhydrous) USP, 1.84 g Sodium Citrate (dihydrate)
USP, 155 mg Monobasic Sodium Phosphate (monohydrate) USP, 2.23 g
Dextrose (monohydrate) USP, 19.3 mg Adenine USP.

STERILE, NON-PYROGENIC
FLUID PATH.
DO NOT USE UNLESS
ANTICOAGULANT IS CLEAR.

NDC:53877-110-06

CODE

LOT NO.

EXPIRY

DONOR NEEDLE 16G × 1½"(1.60 × 38 mm)

UNITS

Rx ONLY

RECOMMENDED STORAGE: Room Temperature (15-30°C/59-86°F).
Avoid excessive heat. Protect from freezing.

After opening, unused bags may be stored at room temperature for 96 hours, or they may be
stored for 30 days in the blister package after returning the cover film to original position and
sealing with tape to prevent possible loss of moisture. See Instructions For Blood Collection.

Manufactured by : TERUMO CORPORATION Tokyo, Japan

All brand names are trademarks or registered trademarks owned by TERUMO CORPORATION,
its affiliates, or unrelated third parties.

Rev. 2024-07
SC-6-H6-H6-A2 ①